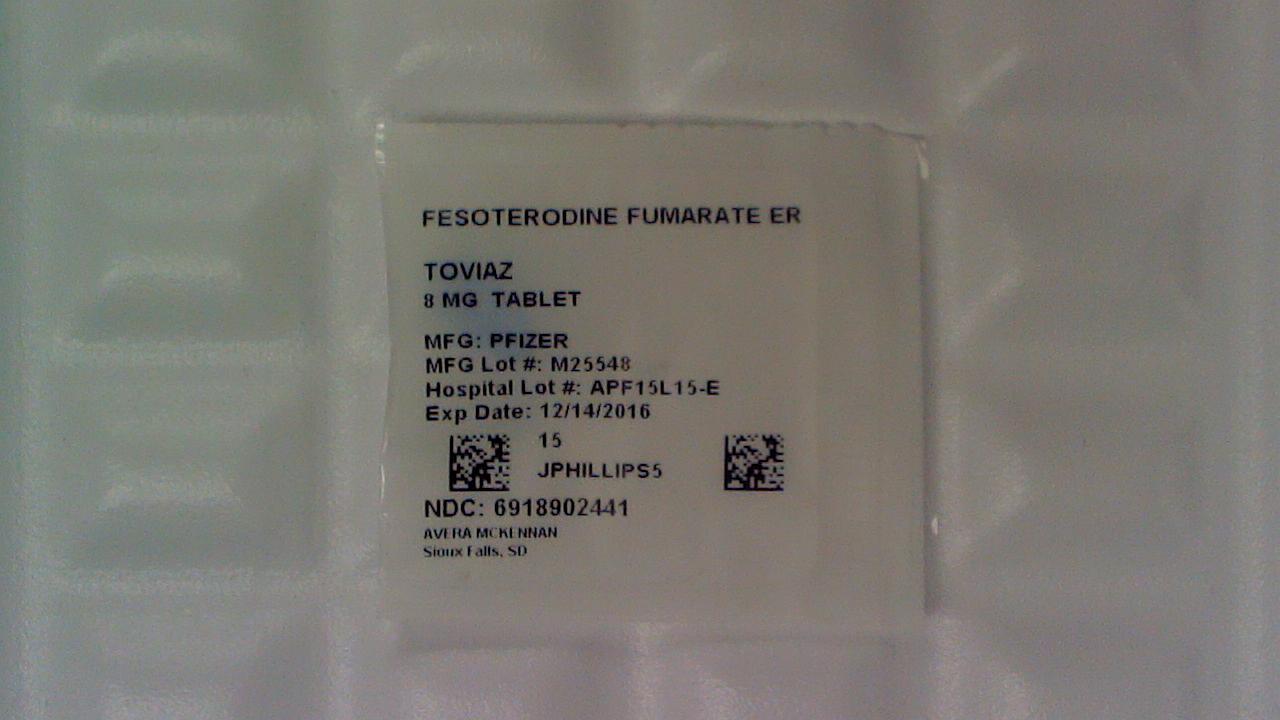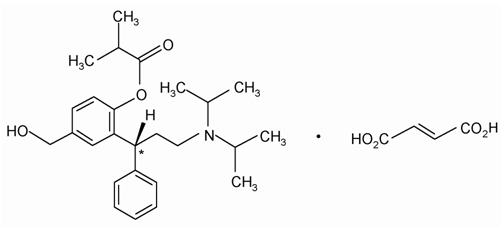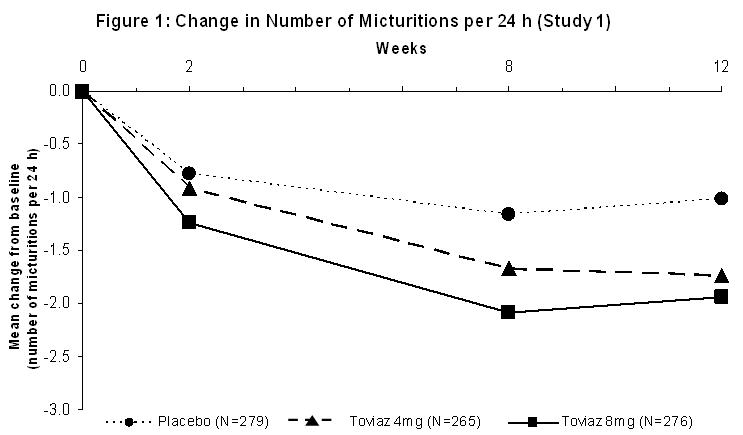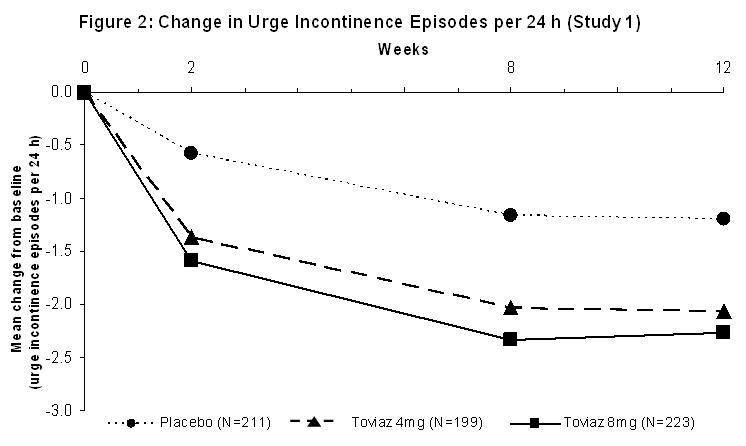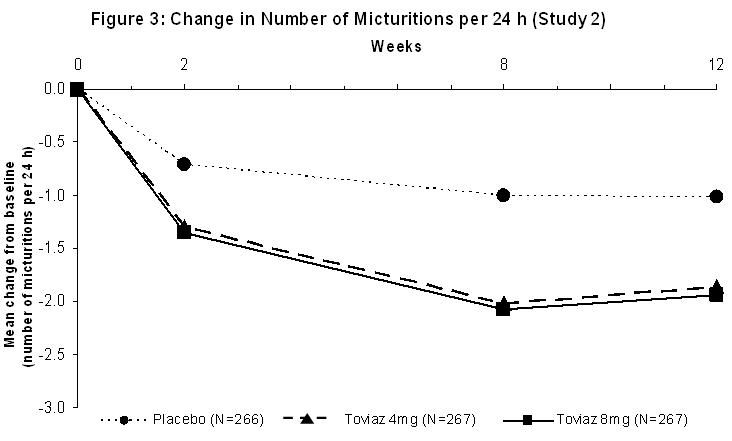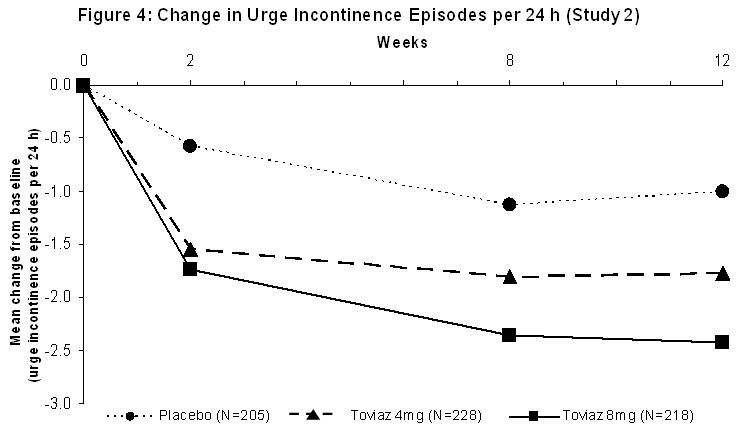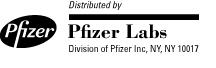 DRUG LABEL: Toviaz
NDC: 69189-0244 | Form: TABLET, FILM COATED, EXTENDED RELEASE
Manufacturer: Avera McKennan Hospital
Category: prescription | Type: HUMAN PRESCRIPTION DRUG LABEL
Date: 20170315

ACTIVE INGREDIENTS: FESOTERODINE FUMARATE 8 mg/1 1
INACTIVE INGREDIENTS: GLYCERYL DIBEHENATE; HYPROMELLOSE, UNSPECIFIED; INDIGOTINDISULFONATE SODIUM; ALUMINUM OXIDE; LACTOSE MONOHYDRATE; LECITHIN, SOYBEAN; MICROCRYSTALLINE CELLULOSE; POLYETHYLENE GLYCOL, UNSPECIFIED; POLYVINYL ALCOHOL, UNSPECIFIED; TALC; TITANIUM DIOXIDE; XYLITOL

HIGHLIGHTS OF PRESCRIBING INFORMATION

These highlights do not include all the information needed to use TOVIAZ safely and effectively. See full prescribing information for TOVIAZ.
Toviaz® (fesoterodine fumarate)
For oral administration
Initial U.S. Approval: 2008

1 INDICATIONS AND USAGE

Toviaz is a muscarinic antagonist indicated for the treatment of overactive bladder with symptoms of urge urinary incontinence, urgency, and frequency. (1)

2 DOSAGE AND ADMINISTRATION

The recommended starting dose of Toviaz is 4 mg once daily. Based upon individual response and tolerability, the dose may be increased to 8 mg once daily. (2)

The daily dose of Toviaz should not exceed 4 mg in the following populations:

- Patients with severe renal impairment (CLCR <30 mL/min) (2)
- Patients taking potent CYP3A4 inhibitors, such as ketoconazole, itraconazole, and clarithromycin. (2)

Toviaz is not recommended for use in patients with severe hepatic impairment (Child-Pugh C). (2)

Toviaz should be taken with liquid and swallowed whole. Toviaz can be administered with or without food, and should not be chewed, divided, or crushed. (2)

3 DOSAGE FORMS AND STRENGTHS

Toviaz 4 mg extended-release tablets are light blue, oval, biconvex, film-coated, and engraved with "FS" on one side. (3)

Toviaz 8 mg extended-release tablets are blue, oval, biconvex, film-coated, and engraved with "FT" on one side. (3)

4 CONTRAINDICATIONS

Toviaz is contraindicated in patients with urinary retention, gastric retention, or uncontrolled narrow-angle glaucoma. Toviaz is also contraindicated in patients with known hypersensitivity to the drug or its ingredients or to tolterodine tartrate tablets or tolterodine tartrate extended-release capsules. (4)

5 WARNINGS AND PRECAUTIONS

- Angioedema of the face, lips, tongue, and/or larynx has been reported with fesoterodine. (5.1).
- Toviaz should be administered with caution to patients with clinically significant bladder outlet obstruction because of the risk of urinary retention. (5.2)
- Toviaz, like other antimuscarinic drugs, should be used with caution in patients with decreased gastrointestinal motility, such as those with severe constipation. (5.3)
- Toviaz should be used with caution in patients being treated for narrow-angle glaucoma, and only where the potential benefits outweigh the risks (5.4)
- Central Nervous System Effects: Somnolence has been reported with Toviaz. Advise patients not to drive or operate heavy machinery until they know how Toviaz affects them (5.5)
- Toviaz should be used with caution in patients with myasthenia gravis, a disease characterized by decreased cholinergic activity at the neuromuscular junction. (5.9)

6 ADVERSE REACTIONS

The most frequently reported adverse events (≥4%) for Toviaz were: dry mouth (placebo, 7%; Toviaz 4 mg, 19%; Toviaz 8 mg, 35%) and constipation (placebo, 2%; Toviaz 4 mg, 4%; Toviaz 8 mg, 6%). (6)

To report SUSPECTED ADVERSE REACTIONS, contact Pfizer Inc at 1-800-438-1985 or FDA at 1-800-FDA-1088 or www.fda.gov/medwatch.

8 USE IN SPECIFIC POPULATIONS

- Pregnancy and Nursing Mothers: Toviaz should be used during pregnancy only if the potential benefit outweighs the potential risk to the fetus. (8.1) Toviaz should not be administered during nursing unless the potential benefit outweighs the potential risk to the neonate. (8.3)
- Pediatric Use: The safety and effectiveness of Toviaz in pediatric patients have not been established. (8.4)

FULL PRESCRIBING INFORMATION

1 INDICATIONS AND USAGE

Toviaz® is a muscarinic antagonist indicated for the treatment of overactive bladder with symptoms of urge urinary incontinence, urgency, and frequency.

2 DOSAGE AND ADMINISTRATION

The recommended starting dose of Toviaz is 4 mg once daily. Based upon individual response and tolerability, the dose may be increased to 8 mg once daily.

The daily dose of Toviaz should not exceed 4 mg in the following populations:

- Patients with severe renal impairment (CLCR <30 mL/min).
- Patients taking potent CYP3A4 inhibitors, such as ketoconazole, itraconazole, and clarithromycin.

Toviaz is not recommended for use in patients with severe hepatic impairment (Child-Pugh C) [see Warnings and Precautions (5.6, 5.8, 5.9); Use in Specific Populations (8.6, 8.7); and Drug Interactions (7.2)].

Toviaz should be taken with liquid and swallowed whole. Toviaz can be administered with or without food, and should not be chewed, divided, or crushed.

3 DOSAGE FORMS AND STRENGTHS

Toviaz (fesoterodine fumarate) extended-release tablets 4 mg are light blue, oval, biconvex, film-coated, and engraved with "FS" on one side.

Toviaz (fesoterodine fumarate) extended-release tablets 8 mg are blue, oval, biconvex, film-coated, and engraved with "FT" on one side.

4 CONTRAINDICATIONS

Toviaz is contraindicated in patients with urinary retention, gastric retention, or uncontrolled narrow-angle glaucoma. Toviaz is also contraindicated in patients with known hypersensitivity to the drug or its ingredients, or to tolterodine tartrate tablets or tolterodine tartrate extended-release capsules [see Clinical Pharmacology (12.1)].

5 WARNINGS AND PRECAUTIONS

5.1 Angioedema

Angioedema of the face, lips, tongue, and/or larynx has been reported with fesoterodine. In some cases angioedema occurred after the first dose. Angioedema associated with upper airway swelling may be life-threatening. If involvement of the tongue, hypopharynx, or larynx occurs, fesoterodine should be promptly discontinued and appropriate therapy and/or measures to ensure a patent airway should be promptly provided.

5.2 Bladder Outlet Obstruction

Toviaz should be administered with caution to patients with clinically significant bladder outlet obstruction because of the risk of urinary retention [see Contraindications (4)].

5.3 Decreased Gastrointestinal Motility

Toviaz, like other antimuscarinic drugs, should be used with caution in patients with decreased gastrointestinal motility, such as those with severe constipation.

5.4 Controlled Narrow-Angle Glaucoma

Toviaz should be used with caution in patients being treated for narrow-angle glaucoma, and only where the potential benefits outweigh the risks [see Contraindications (4)].

5.5 Central Nervous System Effects

Toviaz is associated with anticholinergic central nervous sytem (CNS) effects [see Adverse Reactions (6.2)]. A variety of CNS anticholinergic effects have been reported, including headache, dizziness, and somnolence. Patients should be monitored for signs of anticholinergic CNS effects, particularly after beginning treatment or increasing the dose. Advise patients not to drive or operate heavy machinery until they know how Toviaz affects them. If a patient experiences anticholinergic CNS effects, dose reduction or drug discontinuation should be considered.

5.6 Hepatic Impairment

Toviaz has not been studied in patients with severe hepatic impairment and therefore is not recommended for use in this patient population [see Use in Specific Populations (8.7) and Dosage and Administration (2)].

5.7 Renal Impairment

Doses of Toviaz greater than 4 mg are not recommended in patients with severe renal impairment [see Use In Specific Populations (8.6) and Dosage and Administration (2)].

5.8 Concomitant Administration with CYP3A4 Inhibitors

Doses of Toviaz greater than 4 mg are not recommended in patients taking a potent CYP3A4 inhibitor (e.g., ketoconazole, itraconazole, clarithromycin).

No dosing adjustments are recommended in the presence of moderate CYP3A4 inhibitors (e.g., erythromycin, fluconazole, diltiazem, verapamil and grapefruit juice).

While the effect of weak CYP3A4 inhibitors (e.g. cimetidine) was not examined by clinical study, some pharmacokinetic interaction is expected, albeit less than that observed with moderate CYP3A4 inhibitors [see Drug Interactions (7.2) and Dosage and Administration (2)].

5.9 Myasthenia Gravis

Toviaz should be used with caution in patients with myasthenia gravis, a disease characterized by decreased cholinergic activity at the neuromuscular junction.

6 ADVERSE REACTIONS

6.1 Clinical Trials Experience

The safety of Toviaz was evaluated in Phase 2 and 3 controlled trials in a total of 2859 patients with overactive bladder, of which 2288 were treated with fesoterodine. Of this total, 782 received Toviaz 4 mg/day, and 785 received Toviaz 8 mg/day in Phase 2 or 3 studies with treatment periods of 8 or 12 weeks. Approximately 80% of these patients had >10 weeks exposure to Toviaz in these trials.

A total of 1964 patients participated in two 12-week, Phase 3 efficacy and safety studies and subsequent open-label extension studies. In these two studies combined, 554 patients received Toviaz 4 mg/day and 566 patients received Toviaz 8 mg/day.

In Phase 2 and 3 placebo-controlled trials combined, the incidences of serious adverse events in patients receiving placebo, Toviaz 4 mg, and Toviaz 8 mg were 1.9%, 3.5%, and 2.9%, respectively. All serious adverse events were judged to be not related or unlikely to be related to study medication by the investigator, except for four patients receiving Toviaz who reported one serious adverse event each: angina, chest pain, gastroenteritis, and QT prolongation on ECG.

The most commonly reported adverse event in patients treated with Toviaz was dry mouth. The incidence of dry mouth was higher in those taking 8 mg/day (35%) and in those taking 4 mg/day (19%), as compared to placebo (7%). Dry mouth led to discontinuation in 0.4%, 0.4%, and 0.8% of patients receiving placebo, Toviaz 4 mg, and Toviaz 8 mg, respectively. For those patients who reported dry mouth, most had their first occurrence of the event within the first month of treatment.

The second most commonly reported adverse event was constipation. The incidence of constipation was 2% in those taking placebo, 4% in those taking 4 mg/day, and 6% in those taking 8 mg/day.

Table 1 lists adverse events, regardless of causality, that were reported in the combined Phase 3, randomized, placebo-controlled trials at an incidence greater than placebo and in 1% or more of patients treated with Toviaz 4 or 8 mg once daily for up to 12 weeks.

Table 1: Adverse events with an incidence exceeding the placebo rate and reported by ≥1% of patients from double-blind, placebo-controlled Phase 3 trials of 12 weeks treatment duration
System organ class/Preferred term | Placebo N=554 % | Toviaz 4 mg/day N=554 % | Toviaz 8 mg/day N=566 %
Gastrointestinal disorders
Dry mouth | 7.0 | 18.8 | 34.6
Constipation | 2.0 | 4.2 | 6.0
Dyspepsia | 0.5 | 1.6 | 2.3
Nausea | 1.3 | 0.7 | 1.9
Abdominal pain upper | 0.5 | 1.1 | 0.5
Infections
Urinary tract infection | 3.1 | 3.2 | 4.2
Upper respiratory tract infection | 2.2 | 2.5 | 1.8
Eye disorders
Dry eyes | 0 | 1.4 | 3.7
Renal and urinary disorders
Dysuria | 0.7 | 1.3 | 1.6
Urinary retention | 0.2 | 1.1 | 1.4
Respiratory disorders
Cough | 0.5 | 1.6 | 0.9
Dry throat | 0.4 | 0.9 | 2.3
General disorders
Edema peripheral | 0.7 | 0.7 | 1.2
Musculoskeletal disorders
Back pain | 0.4 | 2.0 | 0.9
Psychiatric disorders
Insomnia | 0.5 | 1.3 | 0.4
Investigations
ALT increased | 0.9 | 0.5 | 1.2
GGT increased | 0.4 | 0.4 | 1.2
Skin disorders
Rash | 0.5 | 0.7 | 1.1
ALT = alanine aminotransferase; GGT = gamma glutamyltransferase

Patients also received Toviaz for up to three years in open-label extension phases of one Phase 2 and two Phase 3 controlled trials. In all open-label trials combined, 857, 701, 529, and 105 patients received Toviaz for at least 6 months, 1 year, 2 years, and 3 years, respectively. The adverse events observed during long-term, open-label studies were similar to those observed in the 12-week, placebo-controlled studies, and included dry mouth, constipation, dry eyes, dyspepsia, and abdominal pain. Similar to the controlled studies, most adverse events of dry mouth and constipation were mild to moderate in intensity. Serious adverse events, judged to be at least possibly related to study medication by the investigator and reported more than once during the open-label treatment period of up to 3 years, included urinary retention (3 cases), diverticulitis (3 cases), constipation (2 cases), irritable bowel syndrome (2 cases), and electrocardiogram QT corrected interval prolongation (2 cases).

6.2 Post-marketing Experience

The following events have been reported in association with fesoterodine use in worldwide post-marketing experience: Eye disorders: Blurred vision; Cardiac disorders: Palpitations; General disorders and administrative site conditions: Hypersensitivity reactions, including angioedema with airway obstruction, face edema; Central nervous system disorders: Dizziness, headache, somnolence; Skin and subcutaneous tissue disorders: Urticaria, pruritus

Because these spontaneously reported events are from the worldwide post-marketing experience, the frequency of events and the role of fesoterodine in their causation cannot be reliably determined.

7 DRUG INTERACTIONS

7.1 Antimuscarinic Drugs

Coadministration of Toviaz with other antimuscarinic agents that produce dry mouth, constipation, urinary retention, and other anticholinergic pharmacological effects may increase the frequency and/or severity of such effects. Anticholinergic agents may potentially alter the absorption of some concomitantly administered drugs due to anticholinergic effects on gastrointestinal motility.

7.2 CYP3A4 Inhibitors

Doses of Toviaz greater than 4 mg are not recommended in patients taking potent CYP3A4 inhibitors, such as ketoconazole, itraconazole, and clarithromycin. Coadministration of the potent CYP3A4 inhibitor ketoconazole with fesoterodine led to approximately a doubling of the maximum concentration (Cmax) and area under the concentration versus time curve (AUC) of 5-hydroxymethyl tolterodine (5-HMT), the active metabolite of fesoterodine. Compared with CYP2D6 extensive metabolizers not taking ketoconazole, further increases in the exposure to 5-HMT were observed in subjects who were CYP2D6 poor metabolizers taking ketoconazole [see Clinical Pharmacology (12.3), Warnings and Precautions (5.8), and Dosage and Administration (2)].

There is no clinically relevant effect of moderate CYP3A4 inhibitors on the pharmacokinetics of fesoterodine. Following blockade of CYP3A4 by coadministration of the moderate CYP3A4 inhibitor fluconazole 200 mg twice a day for 2 days, the average (90% confidence interval) increase in Cmax and AUC of the active metabolite of fesoterodine was approximately 19% (11% – 28%) and 27% (18% – 36%) respectively. No dosing adjustments are recommended in the presence of moderate CYP3A4 inhibitors (e.g., erythromycin, fluconazole, diltiazem, verapamil and grapefruit juice).

The effect of weak CYP3A4 inhibitors (e.g. cimetidine) was not examined; it is not expected to be in excess of the effect of moderate inhibitors [see Clinical Pharmacology (12.3), Warnings and Precautions (5.8), and Dosage and Administration (2)].

7.3 CYP3A4 Inducers

No dosing adjustments are recommended in the presence of CYP3A4 inducers, such as rifampin and carbamazepine. Following induction of CYP3A4 by coadministration of rifampin 600 mg once a day, Cmax and AUC of the active metabolite of fesoterodine decreased by approximately 70% and 75%, respectively, after oral administration of Toviaz 8 mg. The terminal half-life of the active metabolite was not changed.

7.4 CYP2D6 Inhibitors

The interaction with CYP2D6 inhibitors was not tested clinically. In poor metabolizers for CYP2D6, representing a maximum CYP2D6 inhibition, Cmax and AUC of the active metabolite are increased 1.7- and 2-fold, respectively.

No dosing adjustments are recommended in the presence of CYP2D6 inhibitors.

7.5 Drugs Metabolized by Cytochrome P450

In vitro data indicate that at therapeutic concentrations, the active metabolite of fesoterodine does not have the potential to inhibit or induce Cytochrome P450 enzyme systems [see Clinical Pharmacology (12.3)].

7.6 Oral Contraceptives

In the presence of fesoterodine, there are no clinically significant changes in the plasma concentrations of combined oral contraceptives containing ethinyl estradiol and levonorgestrel [see Clinical Pharmacology (12.3)].

7.7 Warfarin

A clinical study has shown that fesoterodine 8 mg once daily has no significant effect on the pharmacokinetics or the anticoagulant activity (PT/INR) of warfarin 25 mg. Standard therapeutic monitoring for warfarin should be continued [see Clinical Pharmacology (12.3)].

7.8 Drug-Laboratory Test Interactions

Interactions between Toviaz and laboratory tests have not been studied.

8 USE IN SPECIFIC POPULATIONS

8.1 Pregnancy

TERATOGENIC EFFECTS

Pregnancy Category C. There are no adequate and well-controlled studies using Toviaz in pregnant women.

No dose-related teratogenicity was observed in reproduction studies performed in mice and rabbits. In mice at 6 to 27 times the expected exposure at the maximum recommended human dose (MRHD) of 8 mg based on AUC (75 mg/kg/day, oral), increased resorptions and decreased live fetuses were observed. One fetus with cleft palate was observed at each dose (15, 45, and 75 mg/kg/day), at an incidence within the background historical range. In rabbits treated at 3 to 11 times the MRHD (27 mg/kg/day, oral), incompletely ossified sternebrae (retardation of bone development) were observed in fetuses. In rabbits at 9 to 11 times the MRHD (4.5 mg/kg/day, subcutaneous), maternal toxicity and incompletely ossified sternebrae were observed in fetuses (at an incidence within the background historical range). In rabbits at 3 times the MRHD (1.5 mg/kg/day, subcutaneous), decreased maternal food consumption in the absence of any fetal effects was observed. Oral administration of 30 mg/kg/day fesoterodine to mice in a pre- and post-natal development study resulted in decreased body weight of the dams and delayed ear opening of the pups. No effects were noted on mating and reproduction of the F1 dams or on the F2 offspring.

Toviaz should be used during pregnancy only if the potential benefit outweighs the potential risk to the fetus.

8.3 Nursing Mothers

It is not known whether fesoterodine is excreted in human milk. Toviaz should not be administered during nursing unless the potential benefit outweighs the potential risk to the neonate.

8.4 Pediatric Use

The pharmacokinetics of fesoterodine have not been evaluated in pediatric patients.

The safety and effectiveness of Toviaz in pediatric patients have not been established.

8.5 Geriatric Use

No dose adjustment is recommended for the elderly. The pharmacokinetics of fesoterodine are not significantly influenced by age.

Of 1567 patients who received Toviaz 4 mg/day or 8 mg/day in the Phase 2 and 3, placebo-controlled, efficacy and safety studies, 515 (33%) were 65 years of age or older, and 140 (9%) were 75 years of age or older. No overall differences in safety or effectiveness were observed between patients younger than 65 years of age and those 65 years of age or older in these studies; however, the incidence of antimuscarinic adverse events, including dry mouth, constipation, dyspepsia, increase in residual urine, dizziness (at 8 mg only) and urinary tract infection, was higher in patients 75 years of age and older as compared to younger patients [see Clinical Studies (14) and Adverse Reactions (6)].

8.6 Renal Impairment

In patients with severe renal impairment (CLCR < 30 mL/min), Cmax and AUC are increased 2.0- and 2.3-fold, respectively. Doses of Toviaz greater than 4 mg are not recommended in patients with severe renal impairment. In patients with mild or moderate renal impairment (CLCR ranging from 30–80 mL/min), Cmax and AUC of the active metabolite are increased up to 1.5- and 1.8-fold, respectively, as compared to healthy subjects. No dose adjustment is recommended in patients with mild or moderate renal impairment [see Warnings and Precautions (5.7) and Dosage and Administration (2)].

8.7 Hepatic Impairment

Patients with severe hepatic impairment (Child-Pugh C) have not been studied; therefore Toviaz is not recommended for use in these patients. In patients with moderate (Child-Pugh B) hepatic impairment, Cmax and AUC of the active metabolite are increased 1.4- and 2.1-fold, respectively, as compared to healthy subjects. No dose adjustment is recommended in patients with mild or moderate hepatic impairment [see Warnings and Precautions (5.6) and Dosage and Administration (2)].

8.8 Gender

No dose adjustment is recommended based on gender. The pharmacokinetics of fesoterodine are not significantly influenced by gender.

8.9 Race

Available data indicate that there are no differences in the pharmacokinetics of fesoterodine between Caucasian and Black healthy subjects following administration of Toviaz.

10 OVERDOSAGE

Overdosage with Toviaz can result in severe anticholinergic effects. Treatment should be symptomatic and supportive. In the event of overdosage, ECG monitoring is recommended.

11 DESCRIPTION

Toviaz contains fesoterodine fumarate and is an extended-release tablet. Fesoterodine is rapidly de-esterified to its active metabolite (R)-2-(3-diisopropylamino-1-phenylpropyl)-4-hydroxymethyl-phenol, or 5-hydroxymethyl tolterodine, which is a muscarinic receptor antagonist.

Chemically, fesoterodine fumarate is designated as isobutyric acid 2-((R)-3-diisopropylammonium-1-phenylpropyl)-4-(hydroxymethyl) phenyl ester hydrogen fumarate. The empirical formula is C30H41NO7 and its molecular weight is 527.66. The structural formula is:

The asterisk (*) indicates the chiral carbon.

Fesoterodine fumarate is a white to off-white powder, which is freely soluble in water. Each Toviaz extended-release tablet contains either 4 mg or 8 mg of fesoterodine fumarate and the following inactive ingredients: glyceryl behenate, hypromellose, indigo carmine aluminum lake, lactose monohydrate, soya lecithin, microcrystalline cellulose, polyethylene glycol, polyvinyl alcohol, talc, titanium dioxide, and xylitol.

12 CLINICAL PHARMACOLOGY

12.1 Mechanism of Action

Fesoterodine is a competitive muscarinic receptor antagonist. After oral administration, fesoterodine is rapidly and extensively hydrolyzed by nonspecific esterases to its active metabolite, 5-hydroxymethyl tolterodine, which is responsible for the antimuscarinic activity of fesoterodine and is also one of the active moieties of tolterodine tartrate tablets and tolterodine tartrate extended-release capsules.

Muscarinic receptors play a role in contractions of urinary bladder smooth muscle and stimulation of salivary secretion. Inhibition of these receptors in the bladder is presumed to be the mechanism by which fesoterodine produces its effects.

12.2 Pharmacodynamics

In a urodynamic study involving patients with involuntary detrusor contractions, the effects after the administration of fesoterodine on the volume at first detrusor contraction and bladder capacity were assessed. Administration of fesoterodine increased the volume at first detrusor contraction and bladder capacity in a dose-dependent manner. These findings are consistent with an antimuscarinic effect on the bladder.

Cardiac Electrophysiology: The effect of fesoterodine 4 mg and 28 mg on the QT interval was evaluated in a double-blind, randomized, placebo- and positive-controlled (moxifloxacin 400 mg once a day) parallel trial with once-daily treatment over a period of 3 days in 261 male and female subjects aged 44 to 65 years. Electrocardiographic parameters were measured over a 24-hour period at pre-dose, after the first administration, and after the third administration of study medication. Fesoterodine 28 mg was chosen because this dose, when administered to CYP2D6 extensive metabolizers, results in an exposure to the active metabolite that is similar to the exposure in a CYP2D6 poor metabolizer receiving fesoterodine 8 mg together with CYP3A4 blockade. Corrected QT intervals (QTc) were calculated using Fridericia's correction and a linear individual correction method. Analyses of 24-hour average QTc, time-matched baseline-corrected QTc, and time-matched placebo-subtracted QTc intervals indicate that fesoterodine at doses of 4 and 28 mg/day did not prolong the QT interval. The sensitivity of the study was confirmed by positive QTc prolongation by moxifloxacin.

Toviaz is associated with an increase in heart rate that correlates with increasing dose. In the study described above, when compared to placebo, the mean increase in heart rate associated with a dose of 4 mg/day and 28 mg/day of fesoterodine was 3 beats/minute and 11 beats/minute, respectively.

In the two, phase 3, placebo-controlled studies in patients with overactive bladder, the mean increase in heart rate compared to placebo was approximately 3–4 beats/minute in the 4 mg/day group and 3–5 beats/minute in the 8 mg/day group.

12.3 Pharmacokinetics

Absorption: After oral administration, fesoterodine is well absorbed. Due to rapid and extensive hydrolysis by nonspecific esterases to its active metabolite 5-hydroxymethyl tolterodine, fesoterodine cannot be detected in plasma. Bioavailability of the active metabolite is 52%. After single or multiple-dose oral administration of fesoterodine in doses from 4 mg to 28 mg, plasma concentrations of the active metabolite are proportional to the dose. Maximum plasma levels are reached after approximately 5 hours. No accumulation occurs after multiple-dose administration.

A summary of pharmacokinetic parameters for the active metabolite after a single dose of Toviaz 4 mg and 8 mg in extensive and poor metabolizers of CYP2D6 is provided in Table 2.

Table 2: Summary of geometric mean [CV] pharmacokinetic parameters for the active metabolite after a single dose of Toviaz 4 mg and 8 mg in extensive and poor CYP2D6 metabolizers
 | Toviaz 4 mg |  | Toviaz 8 mg
Parameter | EM (n=16) | PM (n=8) | EM (n=16) | PM (n=8)
Cmax (ng/mL) | 1.89 [43%] | 3.45 [54%] | 3.98 [28%] | 6.90 [39%]
AUC0–tz (ng*h/mL) | 21.2 [38%] | 40.5 [31%] | 45.3 [32%] | 88.7 [36%]
tmax (h) [Data presented as median (range)] | 5 [2–6] | 5 [5–6] | 5 [3–6] | 5 [5–6]
t½ (h) | 7.31 [27%] | 7.31 [30%] | 8.59 [41%] | 7.66 [21%]
EM = extensive CYP2D6 metabolizer, PM = poor CYP2D6 metabolizer, CV = coefficient of variation
Cmax = maximum plasma concentration, AUC0–tz = area under the concentration time curve from zero up to the last measurable plasma concentration, tmax = time to reach Cmax, t½ = terminal half-life

Effect of Food: There is no clinically relevant effect of food on the pharmacokinetics of fesoterodine. In a study of the effects of food on the pharmacokinetics of fesoterodine in 16 healthy male volunteers, concomitant food intake increased the active metabolite of fesoterodine AUC by approximately 19% and Cmax by 18% [see Dosage and Administration (2)].

Distribution: Plasma protein binding of the active metabolite is low (approximately 50%) and is primarily bound to albumin and alpha-1-acid glycoprotein. The mean steady-state volume of distribution following intravenous infusion of the active metabolite is 169 L.

Metabolism: After oral administration, fesoterodine is rapidly and extensively hydrolyzed to its active metabolite. The active metabolite is further metabolized in the liver to its carboxy, carboxy-N-desisopropyl, and N-desisopropyl metabolites via two major pathways involving CYP2D6 and CYP3A4. None of these metabolites contribute significantly to the antimuscarinic activity of fesoterodine.

Variability in CYP2D6 Metabolism: A subset of individuals (approximately 7% of Caucasians and approximately 2% of African Americans) are poor metabolizers for CYP2D6. Cmax and AUC of the active metabolite are increased 1.7- and 2-fold, respectively, in CYP2D6 poor metabolizers, as compared to extensive metabolizers.

Excretion: Hepatic metabolism and renal excretion contribute significantly to the elimination of the active metabolite. After oral administration of fesoterodine, approximately 70% of the administered dose was recovered in urine as the active metabolite (16%), carboxy metabolite (34%), carboxy-N-desisopropyl metabolite (18%), or N-desisopropyl metabolite (1%), and a smaller amount (7%) was recovered in feces.

The terminal half-life of the active metabolite is approximately 4 hours following an intravenous administration. The apparent terminal half-life following oral administration is approximately 7 hours.

Pharmacokinetics in Specific Populations:

Geriatric Patients: Following a single 8 mg oral dose of fesoterodine, the mean (±SD) AUC and Cmax for the active metabolite 5-hydroxymethyl tolterodine in 12 elderly men (mean age 67 years) were 51.8 ± 26.1 h*ng/mL and 3.8 ± 1.7 ng/mL, respectively. In the same study, the mean (±SD) AUC and Cmax in 12 young men (mean age 30 years) were 52.0 ± 31.5 h*ng/mL and 4.1 ± 2.1 ng/mL, respectively. The pharmacokinetics of fesoterodine were not significantly influenced by age [see Use in Specific Populations (8.5)].

Pediatric Patients: The pharmacokinetics of fesoterodine have not been evaluated in pediatric patients [see Use in Specific Populations (8.4)].

Gender: Following a single 8 mg oral dose of fesoterodine, the mean (±SD) AUC and Cmax for the active metabolite 5-hydroxymethyl tolterodine in 12 elderly men (mean age 67 years) were 51.8 ± 26.1 h*ng/mL and 3.8 ± 1.7 ng/mL, respectively. In the same study, the mean (±SD) AUC and Cmax in 12 elderly women (mean age 68 years) were 56.0 ± 28.8 h*ng/mL and 4.6 ± 2.3 ng/mL, respectively. The pharmacokinetics of fesoterodine were not significantly influenced by gender [see Use in Specific Populations (8.8)].

Race: The effects of Caucasian or Black race on the pharmacokinetics of fesoterodine were examined in a study of 12 Caucasian and 12 Black African young male volunteers. Each subject received a single oral dose of 8 mg fesoterodine. The mean (±SD) AUC and Cmax for the active metabolite 5-hydroxymethyl tolterodine in Caucasian males were 73.0 ± 27.8 h*ng/mL and 6.1 ± 2.7 ng/mL, respectively. The mean (±SD) AUC and Cmax in Black males were 65.8 ± 23.2 h*ng/mL and 5.5 ± 1.9 ng/mL, respectively. The pharmacokinetics of fesoterodine were not significantly influenced by race [see Use in Specific Populations (8.9)].

Renal Impairment: In patients with mild or moderate renal impairment (CLCR ranging from 30–80 mL/min), Cmax and AUC of the active metabolite are increased up to 1.5- and 1.8-fold, respectively, as compared to healthy subjects. In patients with severe renal impairment (CLCR < 30 mL/min), Cmax and AUC are increased 2.0- and 2.3-fold, respectively. [see Use in Specific Populations (8.6), Warnings and Precautions (5.7), and Dosage and Administration (2)].

Hepatic Impairment: In patients with moderate (Child-Pugh B) hepatic impairment, Cmax and AUC of the active metabolite are increased 1.4- and 2.1-fold, respectively, as compared to healthy subjects.

Subjects with severe hepatic impairment (Child-Pugh C) have not been studied [see Use in Specific Populations (8.7), Warnings and Precautions (5.6), and Dosage and Administration (2)].

Drug-Drug Interactions:

Drugs Metabolized by Cytochrome P450: At therapeutic concentrations, the active metabolite of fesoterodine does not inhibit CYP1A2, 2B6, 2C8, 2C9, 2C19, 2D6, 2E1, or 3A4, or induce CYP1A2, 2B6, 2C9, 2C19, or 3A4 in vitro [see Drug Interactions (7.5)].

CYP3A4 Inhibitors: Following blockade of CYP3A4 by coadministration of the potent CYP3A4 inhibitor ketoconazole 200 mg twice a day for 5 days, Cmax and AUC of the active metabolite of fesoterodine increased 2.0- and 2.3-fold, respectively, after oral administration of Toviaz 8 mg to CYP2D6 extensive metabolizers. In CYP2D6 poor metabolizers, Cmax and AUC of the active metabolite of fesoterodine increased 2.1- and 2.5-fold, respectively, during coadministration of ketoconazole 200 mg twice a day for 5 days. Cmax and AUC were 4.5- and 5.7-fold higher, respectively, in subjects who were CYP2D6 poor metabolizers and taking ketoconazole compared to subjects who were CYP2D6 extensive metabolizers and not taking ketoconazole. In a separate study coadministering fesoterodine with ketoconazole 200 mg once a day for 5 days, the Cmax and AUC values of the active metabolite of fesoterodine were increased 2.2-fold in CYP2D6 extensive metabolizers and 1.5- and 1.9-fold, respectively, in CYP2D6 poor metabolizers. Cmax and AUC were 3.4- and 4.2-fold higher, respectively, in subjects who were CYP2D6 poor metabolizers and taking ketoconazole compared to subjects who were CYP2D6 extensive metabolizers and not taking ketoconazole.

There is no clinically relevant effect of moderate CYP3A4 inhibitors on the pharmacokinetics of fesoterodine. In a drug-drug interaction study evaluating the coadministration of the moderate CYP3A4 inhibitor fluconazole 200 mg twice a day for 2 days, a single 8 mg dose of fesoterodine was administered 1 hour following the first dose of fluconazole on day 1 of the study. The average (90% confidence interval) for the increase in Cmax and AUC of the active metabolite of fesoterodine was approximately 19% (11% – 28%) and 27% (18% – 36%) respectively.

The effect of weak CYP3A4 inhibitors (e.g. cimetidine) was not examined; it is not expected to be in excess of the effect of moderate inhibitors [see Drug Interactions (7.2)], Warnings and Precautions (5.8), and Dosage and Administration (2)].

CYP3A4 Inducers: Following induction of CYP3A4 by coadministration of rifampicin 600 mg once a day, Cmax and AUC of the active metabolite of fesoterodine decreased by approximately 70% and 75%, respectively, after oral administration of Toviaz 8 mg. The terminal half-life of the active metabolite was not changed.

Induction of CYP3A4 may lead to reduced plasma levels. No dosing adjustments are recommended in the presence of CYP3A4 inducers [see Drug Interactions (7.3)].

CYP2D6 Inhibitors: The interaction with CYP2D6 inhibitors was not studied. In poor metabolizers for CYP2D6, representing a maximum CYP2D6 inhibition, Cmax and AUC of the active metabolite are increased 1.7- and 2-fold, respectively. [see Drug Interactions (7.4)].

Oral Contraceptives: Thirty healthy female subjects taking an oral contraceptive containing 0.03 mg ethinyl estradiol and 0.15 mg levonorgestrel were evaluated in a 2-period crossover study. Each subject was randomized to receive concomitant administration of either placebo or fesoterodine 8 mg once daily on days 1 – 14 of hormone cycle for 2 consecutive cycles. Pharmacokinetics of ethinyl estradiol and levonorgestrel were assessed on day 13 of each cycle. Fesoterodine increased the AUC and Cmax of ethinyl estradiol by 1 – 3% and decreased the AUC and Cmax of levonorgestrel by 11 – 13% [see Drug Interactions (7.6)].

Warfarin: In a cross-over study in 14 healthy male volunteers (18–55 years), a single oral dose of warfarin 25 mg was given either alone or on day 3 of once daily dosing for 9 days with fesoterodine 8 mg. Compared to warfarin alone dosing, the Cmax and AUC of S-warfarin were lower by ~ 4 %, while the Cmax and AUC of R-warfarin were lower by approximately 8 % and 6% for the co-administration, suggesting absence of a significant pharmacokinetic interaction.

There were no statistically significant changes in the measured pharmacodynamic parameters for anti-coagulant activity of warfarin (INRmax, AUCINR), with only a small decrease noted in INRmax of ~ 3 % with the co-administration relative to warfarin alone. INR versus time profiles across individual subjects in the study suggested some differences following co-administration with fesoterodine, although there was no definite trend with regard to the changes noted [see Drug Interactions (7.7)].

13 NONCLINICAL TOXICOLOGY

13.1 Carcinogenesis, Mutagenesis, Impairment of Fertility

No evidence of drug-related carcinogenicity was found in 24-month studies with oral administration to mice and rats. The highest tolerated doses in mice (females 45 to 60 mg/kg/day, males 30 to 45 mg/kg/day) correspond to 11 to 19 times (females) and 4 to 9 times (males) the estimated human AUC values reached with fesoterodine 8 mg, which is the Maximum Recommended Human Dose (MRHD). In rats, the highest tolerated dose (45 to 60 mg/kg/day) corresponds to 3 to 8 times (females) and 3 to 14 times (males) the estimated human AUC at the MRHD.

Fesoterodine was not mutagenic or genotoxic in vitro (Ames tests, chromosome aberration tests) or in vivo (mouse micronucleus test).

Fesoterodine had no effect on reproductive function, fertility, or early embryonic development of the fetus at non-maternally toxic doses in mice. The maternal No-Observed-Effect Level (NOEL) and the NOEL for effects on reproduction and early embryonic development were both 15 mg/kg/day. Based on AUC, the systemic exposure was 0.6 to 1.5 times higher in mice than in humans at the MRHD, whereas based on peak plasma concentrations, the exposure in mice was 5 to 9 times higher. The Lowest-Observed-Effect Level (LOEL) for maternal toxicity was 45 mg/kg/day.

14 CLINICAL STUDIES

Toviaz extended-release tablets were evaluated in two, Phase 3, randomized, double-blind, placebo-controlled, 12-week studies for the treatment of overactive bladder with symptoms of urge urinary incontinence, urgency, and urinary frequency. Entry criteria required that patients have symptoms of overactive bladder for ≥ 6-months duration, at least 8 micturitions per day, and at least 6 urinary urgency episodes or 3 urge incontinence episodes per 3-day diary period. Patients were randomized to a fixed dose of Toviaz 4 or 8 mg/day or placebo. In one of these studies, 290 patients were randomized to an active control arm (an oral antimuscarinic agent). For the combined studies, a total of 554 patients received placebo, 554 patients received Toviaz 4 mg/day, and 566 patients received Toviaz 8 mg/day. The majority of patients were Caucasian (91%) and female (79%) with a mean age of 58 years (range 19–91 years).

The primary efficacy endpoints were the mean change in the number of urge urinary incontinence episodes per 24 hours and the mean change in the number of micturitions (frequency) per 24 hours. An important secondary endpoint was the mean change in the voided volume per micturition.

Results for the primary endpoints and for mean change in voided volume per micturition from the two 12-week clinical studies of Toviaz are reported in Table 3.

Table 3: Mean baseline and change from baseline to Week 12 for urge urinary incontinence episodes, number of micturitions, and volume voided per micturition
 | Study 1 |  |  | Study 2
Parameter | Placebo N=279 | Toviaz 4mg/day N=265 | Toviaz 8mg/day N=276 | Placebo N=266 | Toviaz 4mg/day N=267 | Toviaz 8mg/day N=267
Number of urge incontinence episodes per 24 hours [Only those patients who were urge incontinent at baseline were included for the analysis of number of urge incontinence episodes per 24 hours: In Study 1, the number of these patients was 211, 199, and 223 in the placebo, Toviaz 4 mg/day and Toviaz 8 mg/day groups, respectively. In Study 2, the number of these patients was 205, 228, and 218, respectively.]
Baseline | 3.7 | 3.8 | 3.7 | 3.7 | 3.9 | 3.9
Change from baseline | -1.20 | -2.06 | -2.27 | -1.00 | -1.77 | -2.42
p-value vs. placebo | - | 0.001 | <0.001 | - | <0.003 | <0.001
Number of micturitions per 24 hours
Baseline | 12.0 | 11.6 | 11.9 | 12.2 | 12.9 | 12.0
Change from baseline | -1.02 | -1.74 | -1.94 | -1.02 | -1.86 | -1.94
p-value vs. placebo | - | <0.001 | <0.001 | - | 0.032 | <0.001
Voided volume per micturition (mL)
Baseline | 150 | 160 | 154 | 159 | 152 | 156
Change from baseline | 10 | 27 | 33 | 8 | 17 | 33
p-value vs. placebo | - | <0.001 | <0.001 | - | 0.150 | <0.001
vs. = versus

Figures 1–4: The following figures show change from baseline over time in number of micturitions and urge urinary incontinence episodes per 24 h in the two studies.

A reduction in number of urge urinary incontinence episodes per 24 hours was observed for both doses as compared to placebo as early as two weeks after starting Toviaz therapy.

16 HOW SUPPLIED/STORAGE AND HANDLING

Toviaz (fesoterodine fumarate) extended-release tablets 8 mg are blue, oval, biconvex, film-coated, and engraved with "FT" on one side. They are supplied as follows:

NDC 69189-0244-1 single dose pack with 1 tablet as repackaged by Avera McKennan Hospital

Bottles of 30 | NDC 0069-0244-30

STORAGE AND HANDLING

Store at 20° to 25°C (68° to 77°F); excursions permitted between 15° to 30°C (59° to 86°F) [see USP Controlled Room Temperature]. Protect from moisture.

17 PATIENT COUNSELING INFORMATION

See FDA-Approved Patient Labeling (17.2)

17.1 Information for Patients

Patients should be informed that fesoterodine may produce angioedema, which could result in life-threatening airway obstruction. Patients should be advised to promptly discontinue fesoterodine therapy and seek immediate medical attention if they experience edema of the tongue or laryngopharynx, or difficult breathing.

Patients should be informed that Toviaz, like other antimuscarinic agents, may produce clinically significant adverse effects related to antimuscarinic pharmacological activity including constipation and urinary retention. Toviaz, like other antimuscarinics, may be associated with blurred vision, therefore, patients should be advised to exercise caution in decisions to engage in potentially dangerous activities until the drug's effects on the patient have been determined. Heat prostration (due to decreased sweating) can occur when Toviaz, like other antimuscarinic drugs, is used in a hot environment.

Patients should also be informed that alcohol may enhance the drowsiness caused by Toviaz, like other anticholinergic agents. Patients should read the patient leaflet entitled "Patient Information TOVIAZ" before starting therapy with Toviaz.

Patient Information
TOVIAZ® (TOH-vee-as)
(fesoterodine fumarate)
extended-release tablets

Read the Patient Information that comes with TOVIAZ before you start taking it and each time you get a refill. There may be new information. This leaflet does not take the place of talking with your doctor about your medical condition or your treatment.

What is TOVIAZ?

TOVIAZ is a prescription medicine used in adults to treat symptoms of a condition called overactive bladder, including:

- Urge urinary incontinence -- leaking or wetting accidents due to a strong need to urinate,
- Urinary urgency -- having a strong need to urinate right away,
- Urinary frequency -- having to urinate too often.

TOVIAZ has not been studied in children.

Who should not take TOVIAZ?

Do not take TOVIAZ if you:

- Are not able to empty your bladder (urinary retention)
- Have delayed or slow emptying of your stomach (gastric retention)
- Have an eye problem called "uncontrolled narrow-angle glaucoma"
- Are allergic to TOVIAZ or any of its ingredients. See the end of this leaflet for a complete list of ingredients
- Are allergic to Detrol® or Detrol® LA, which contains tolterodine.

What should I tell my doctor before starting TOVIAZ?

Before starting TOVIAZ, tell your doctor about all of your medical and other conditions that may affect the use of TOVIAZ, including:

- Stomach or intestinal problems or problems with constipation
- Problems emptying your bladder or if you have a weak urine stream
- Treatment for an eye problem called narrow-angle glaucoma
- Kidney problems
- Liver problems
- A condition called myasthenia gravis
- If you are pregnant or trying to become pregnant. It is not known if TOVIAZ can harm your unborn baby.
- If you are breastfeeding. It is not known if TOVIAZ passes into breast milk or if it can harm your baby. Talk to your doctor about the best way to feed your baby if you take TOVIAZ.

Before starting on TOVIAZ, tell your doctor about all the medicines you take, including prescription and nonprescription medicines, vitamins, and herbal products. TOVIAZ may affect the way other medicines work, and other medicines may affect how TOVIAZ works. Especially tell your doctor if you are taking antibiotics or antifungal medicines.

Know all the medicines you take. Keep a list of them with you to show your doctor and pharmacist each time you get a new medicine.

How should I take TOVIAZ?

- Take TOVIAZ exactly as your doctor tells you to take it.
- Your doctor may give you the lower 4 mg dose of TOVIAZ if you have certain medical conditions, such as severe kidney problems.
- Take TOVIAZ with liquid and swallow the tablet whole. Do not chew, divide, or crush the tablet.
- You can take TOVIAZ with or without food.
- If you miss a dose of TOVIAZ, begin taking TOVIAZ again the next day. Do not take 2 doses of TOVIAZ in the same day.

If you take too much TOVIAZ, call your doctor or go to an emergency department right away.

What are the possible side effects of TOVIAZ?

TOVIAZ may cause allergic reactions that may be serious. Symptoms of a serious allergic reaction may include swelling of the face, lips, throat or tongue. If you experience these symptoms, you should stop taking TOVIAZ and get emergency medical help right away.

The most common side effects of TOVIAZ are:

- Dry mouth
- Constipation

TOVIAZ may cause other less common side effects, including:

- Dry eyes
- Trouble emptying the bladder

Tell your doctor if you have any side effects that bother you or that do not go away.

Call your doctor for medical advice about side effects. You may report side effects to the FDA at 1-800-FDA-1088.

These are not all of the possible side effects of TOVIAZ. For a complete list, ask your doctor.

What else should I keep in mind while taking TOVIAZ?

- Do not drive, operate machinery, or do other dangerous activities until you know how TOVIAZ affects you. Blurred vision, dizziness, and drowsiness are possible side effects of medicines such as TOVIAZ.
- Use caution in hot environments. Decreased sweating and severe heat illness can occur when medicines such as TOVIAZ are used in a hot environment.
- Drinking alcohol while taking medicines such as TOVIAZ may cause increased drowsiness.

How should I store TOVIAZ?

- Store TOVIAZ at room temperature, 68° to 77°F (20° to 25°C); brief periods permitted between 59° to 86°F (15° to 30°C)
- Protect the medicine from moisture by keeping the bottle closed tightly.
- Safely throw away TOVIAZ that is out of date or no longer needed.

Keep TOVIAZ and all medicines out of the reach of children.

General information about TOVIAZ

Medicines are sometimes prescribed for conditions that are not mentioned in patient information leaflets. Only use TOVIAZ the way your doctor tells you. Do not give TOVIAZ to other people, even if they have the same symptoms you have. It may harm them.

This leaflet summarizes the most important information about TOVIAZ. If you would like more information, talk with your doctor. You can ask your doctor for information about TOVIAZ that is written for healthcare professionals. You can also call 1-877-9-TOVIAZ (1-877-986-8429) or go to www.TOVIAZ.com.

What are the ingredients in TOVIAZ?

Active ingredient: fesoterodine fumarate

Inactive ingredients: glyceryl behenate, hypromellose, indigo carmine aluminum lake, lactose monohydrate, soya lecithin, microcrystalline cellulose, polyethylene glycol, polyvinyl alcohol, talc, titanium dioxide, and xylitol.

This product's label may have been updated. For current full prescribing information, please visit www.pfizer.com.

LAB-0381-14.0

Patient Information
TOVIAZ® (TOH-vee-as)
(fesoterodine fumarate)
extended-release tablets

Read the Patient Information that comes with TOVIAZ before you start taking it and each time you get a refill. There may be new information. This leaflet does not take the place of talking with your doctor about your medical condition or your treatment.

What is TOVIAZ?

TOVIAZ is a prescription medicine used in adults to treat symptoms of a condition called overactive bladder, including:

- Urge urinary incontinence -- leaking or wetting accidents due to a strong need to urinate,
- Urinary urgency -- having a strong need to urinate right away,
- Urinary frequency -- having to urinate too often.

TOVIAZ has not been studied in children.

Who should not take TOVIAZ?

Do not take TOVIAZ if you:

- Are not able to empty your bladder (urinary retention)
- Have delayed or slow emptying of your stomach (gastric retention)
- Have an eye problem called "uncontrolled narrow-angle glaucoma"
- Are allergic to TOVIAZ or any of its ingredients. See the end of this leaflet for a complete list of ingredients
- Are allergic to Detrol® or Detrol® LA, which contains tolterodine.

What should I tell my doctor before starting TOVIAZ?

Before starting TOVIAZ, tell your doctor about all of your medical and other conditions that may affect the use of TOVIAZ, including:

- Stomach or intestinal problems or problems with constipation
- Problems emptying your bladder or if you have a weak urine stream
- Treatment for an eye problem called narrow-angle glaucoma
- Kidney problems
- Liver problems
- A condition called myasthenia gravis
- If you are pregnant or trying to become pregnant. It is not known if TOVIAZ can harm your unborn baby.
- If you are breastfeeding. It is not known if TOVIAZ passes into breast milk or if it can harm your baby. Talk to your doctor about the best way to feed your baby if you take TOVIAZ.

Before starting on TOVIAZ, tell your doctor about all the medicines you take, including prescription and nonprescription medicines, vitamins, and herbal products. TOVIAZ may affect the way other medicines work, and other medicines may affect how TOVIAZ works. Especially tell your doctor if you are taking antibiotics or antifungal medicines.

Know all the medicines you take. Keep a list of them with you to show your doctor and pharmacist each time you get a new medicine.

How should I take TOVIAZ?

- Take TOVIAZ exactly as your doctor tells you to take it.
- Your doctor may give you the lower 4 mg dose of TOVIAZ if you have certain medical conditions, such as severe kidney problems.
- Take TOVIAZ with liquid and swallow the tablet whole. Do not chew, divide, or crush the tablet.
- You can take TOVIAZ with or without food.
- If you miss a dose of TOVIAZ, begin taking TOVIAZ again the next day. Do not take 2 doses of TOVIAZ in the same day.

If you take too much TOVIAZ, call your doctor or go to an emergency department right away.

What are the possible side effects of TOVIAZ?

TOVIAZ may cause allergic reactions that may be serious. Symptoms of a serious allergic reaction may include swelling of the face, lips, throat or tongue. If you experience these symptoms, you should stop taking TOVIAZ and get emergency medical help right away.

The most common side effects of TOVIAZ are:

- Dry mouth
- Constipation

TOVIAZ may cause other less common side effects, including:

- Dry eyes
- Trouble emptying the bladder

Tell your doctor if you have any side effects that bother you or that do not go away.

Call your doctor for medical advice about side effects. You may report side effects to the FDA at 1-800-FDA-1088.

These are not all of the possible side effects of TOVIAZ. For a complete list, ask your doctor.

What else should I keep in mind while taking TOVIAZ?

- Do not drive, operate machinery, or do other dangerous activities until you know how TOVIAZ affects you. Blurred vision, dizziness, and drowsiness are possible side effects of medicines such as TOVIAZ.
- Use caution in hot environments. Decreased sweating and severe heat illness can occur when medicines such as TOVIAZ are used in a hot environment.
- Drinking alcohol while taking medicines such as TOVIAZ may cause increased drowsiness.

How should I store TOVIAZ?

- Store TOVIAZ at room temperature, 68° to 77°F (20° to 25°C); brief periods permitted between 59° to 86°F (15° to 30°C)
- Protect the medicine from moisture by keeping the bottle closed tightly.
- Safely throw away TOVIAZ that is out of date or no longer needed.

Keep TOVIAZ and all medicines out of the reach of children.

General information about TOVIAZ

Medicines are sometimes prescribed for conditions that are not mentioned in patient information leaflets. Only use TOVIAZ the way your doctor tells you. Do not give TOVIAZ to other people, even if they have the same symptoms you have. It may harm them.

This leaflet summarizes the most important information about TOVIAZ. If you would like more information, talk with your doctor. You can ask your doctor for information about TOVIAZ that is written for healthcare professionals. You can also call 1-877-9-TOVIAZ (1-877-986-8429) or go to www.TOVIAZ.com.

What are the ingredients in TOVIAZ?

Active ingredient: fesoterodine fumarate

Inactive ingredients: glyceryl behenate, hypromellose, indigo carmine aluminum lake, lactose monohydrate, soya lecithin, microcrystalline cellulose, polyethylene glycol, polyvinyl alcohol, talc, titanium dioxide, and xylitol.

This product's label may have been updated. For current full prescribing information, please visit www.pfizer.com

LAB-0382-11.0
January 2014